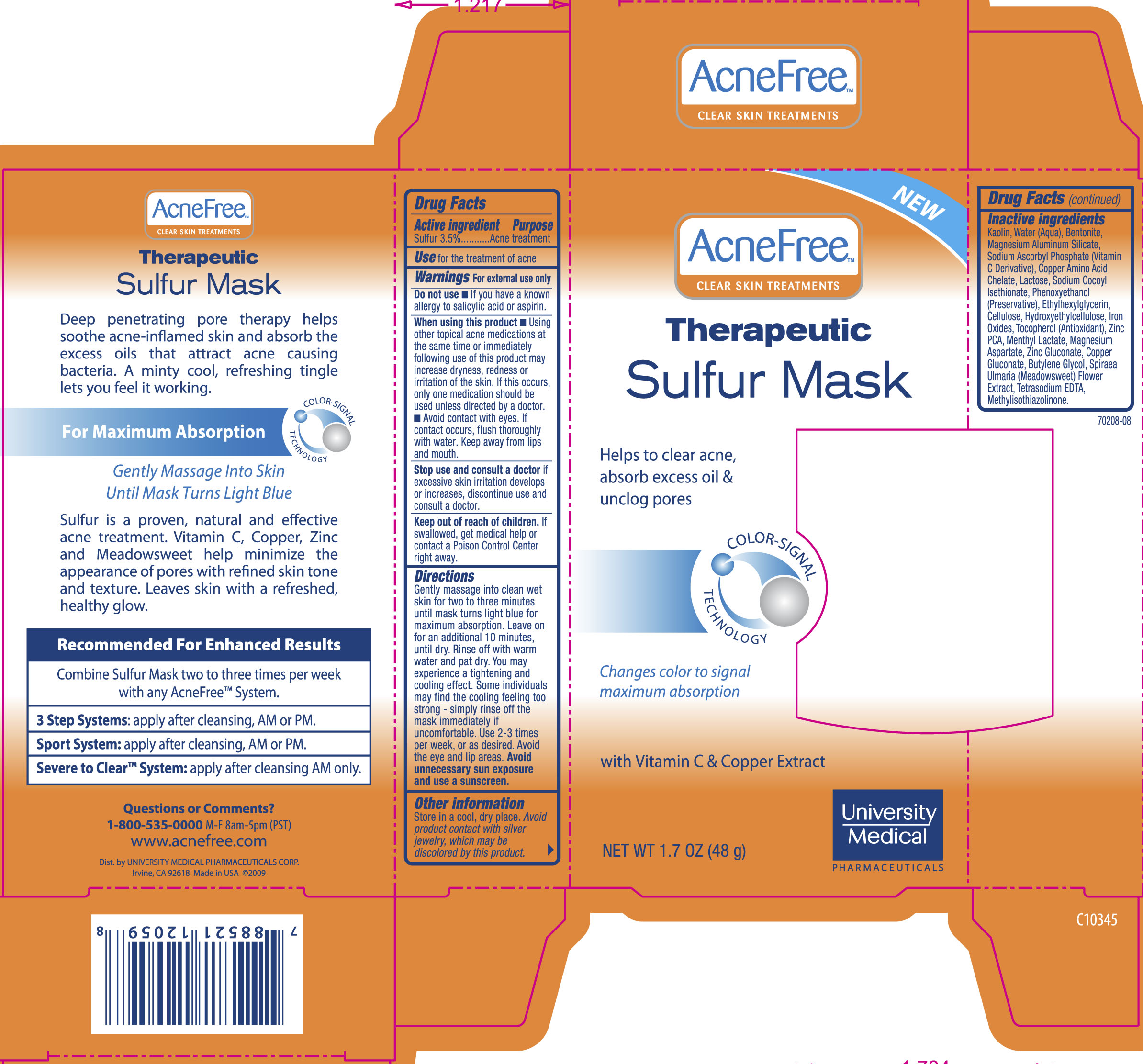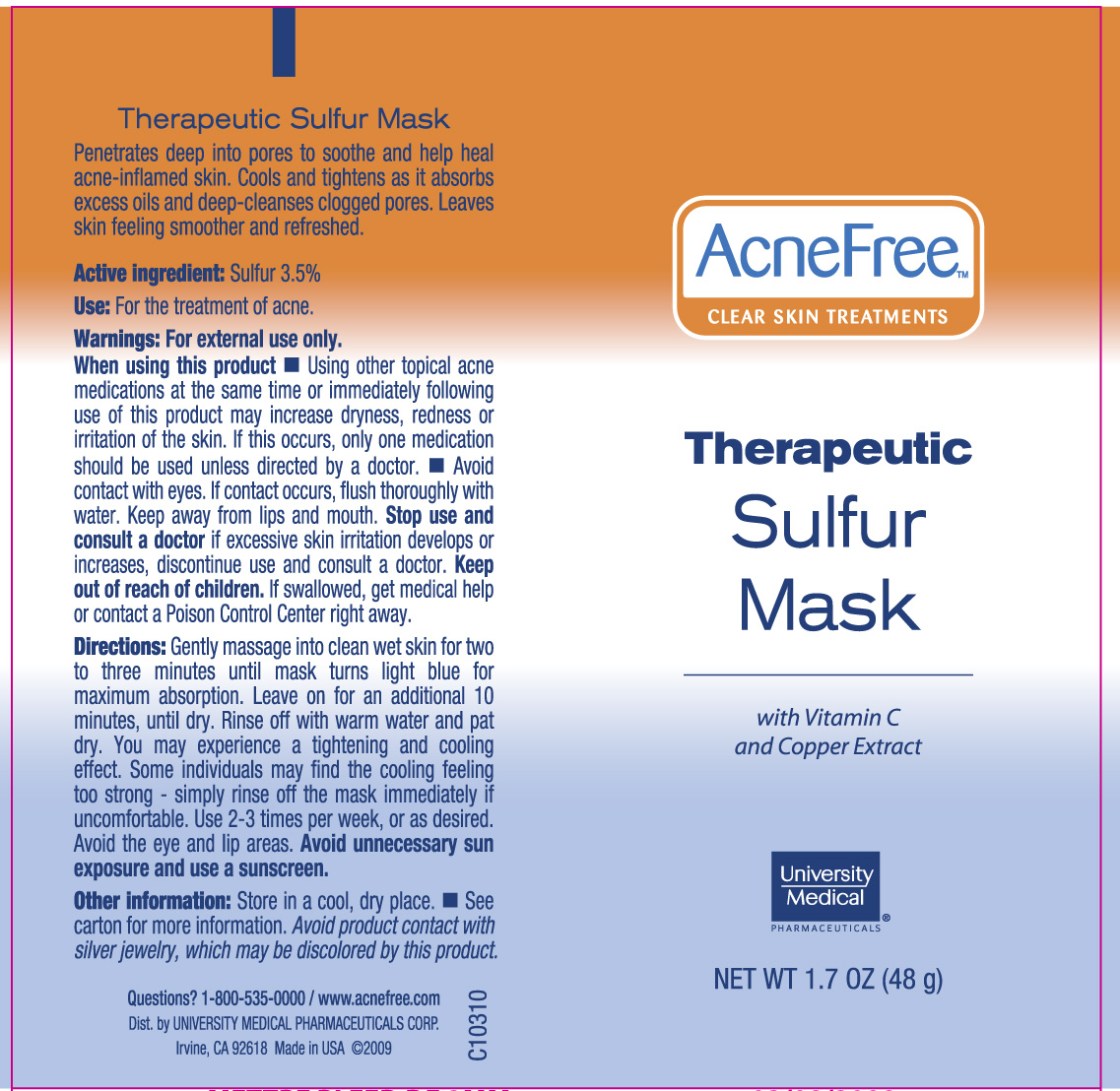 DRUG LABEL: Therapeutic Sulfur Mask
NDC: 50544-004 | Form: CREAM
Manufacturer: University Medical Pharmaceuticals Corp
Category: otc | Type: HUMAN OTC DRUG LABEL
Date: 20110912

ACTIVE INGREDIENTS: Sulfur 35 g/1000 g
INACTIVE INGREDIENTS: water; kaolin; bentonite; MAGNESIUM ALUMINUM SILICATE; titanium dioxide; ACACIA; SODIUM ASCORBYL PHOSPHATE; SODIUM COCOYL ISETHIONATE; ethylhexylglycerin; HYDROXYPROPYL CELLULOSE; menthyl lactate; MAGNESIUM STEARATE; ZINC GLUCONATE; COPPER GLUCONATE; butylene glycol; mannitol; EDETATE SODIUM; magnesium aspartate; METHYLISOTHIAZOLINONE; phenoxyethanol

Drug Facts

Active Ingredient Purpose
Sulfur 3.5%...................................................................................................................................Acne Treatment

INDICATIONS AND USAGE

Use for the treatment of acne

Warnings For external use only

Do not use

- If you have a known allergy to salicylic acid or aspirin.

When using this product

- Using other topical acne medications at the same time or immediately following use of this product may increase dryness, redness or irritation of the skin. If this occurs, only one medication should be used unless directed by a doctor.
- Avoid contact with lips and mouth. Do not get into eyes. If contact occurs, flush thoroughly with water. Keep away from lips and mouth.

Stop use and consult a doctor if excessive skin irritation develops or increases, discontinue use and consult a doctor.

Keep out of reach of children. If swallowed, get medical help or contact a Poison Control Center right away.

Directions
Gently massage into clean wet skin for two to three minutes until mask turns light blue for maximum absorption. Leave on for an additional 10 minutes, until dry. Rinse off with warm water and pat dry. You may experience a tightening and cooling effect. Some individuals may find the cooling feeling too strong - simply rinse off the mask immediately if uncomfortable. Use 2-3 times per week, or as desired. Avoid eye and lip areas. Avoid unnecessary sun exposure and use a sunscreen.

Inactive Ingredients
Acacia Senegal Gum, Bentonite, Butylene Glycol, Cellulose, Copper Gluconate, Ethylhexylglycerin, Hydroxypropyl Methylcellulose, Kaolin, Magnesium Aluminum Silicate, Magnesium Aspartate, Magnesium Stearate, Mannitol, Menthyl Lactate, Methylisothiazolinone, Phenoxyethanol, Soidum Ascobyl Phosphate, Sodium Cocoyl Isethionate, Spiraea Ulmaria Flower Extract, Tetrasodium EDTA, Titanium Dioxide, Ultramarines (CI 77007), Water/Aqua/Eau, Zinc PCA.

Purpose: Acne Treatment

PACKAGE LABEL

AcneFree Clear Skin Treatments